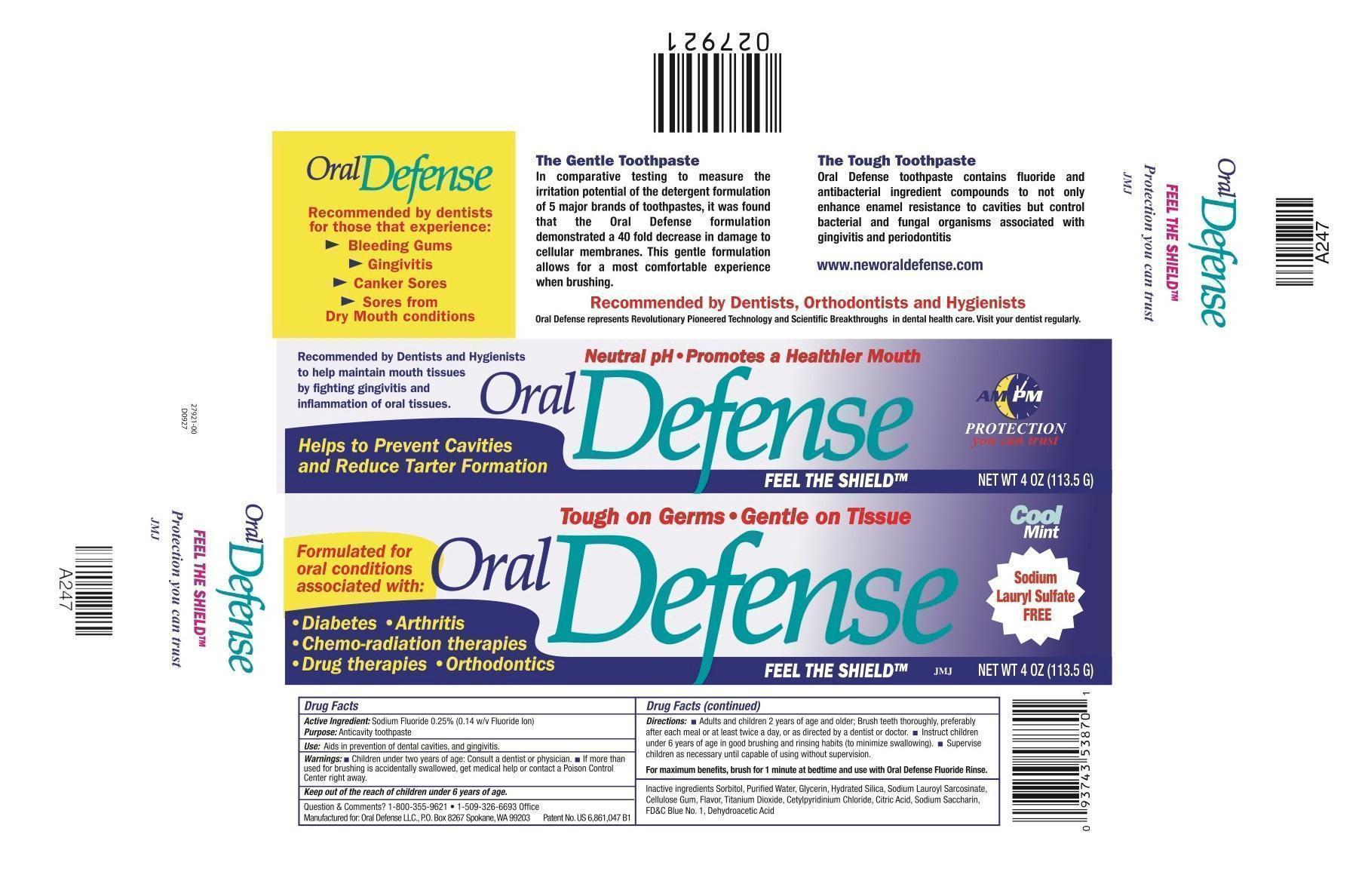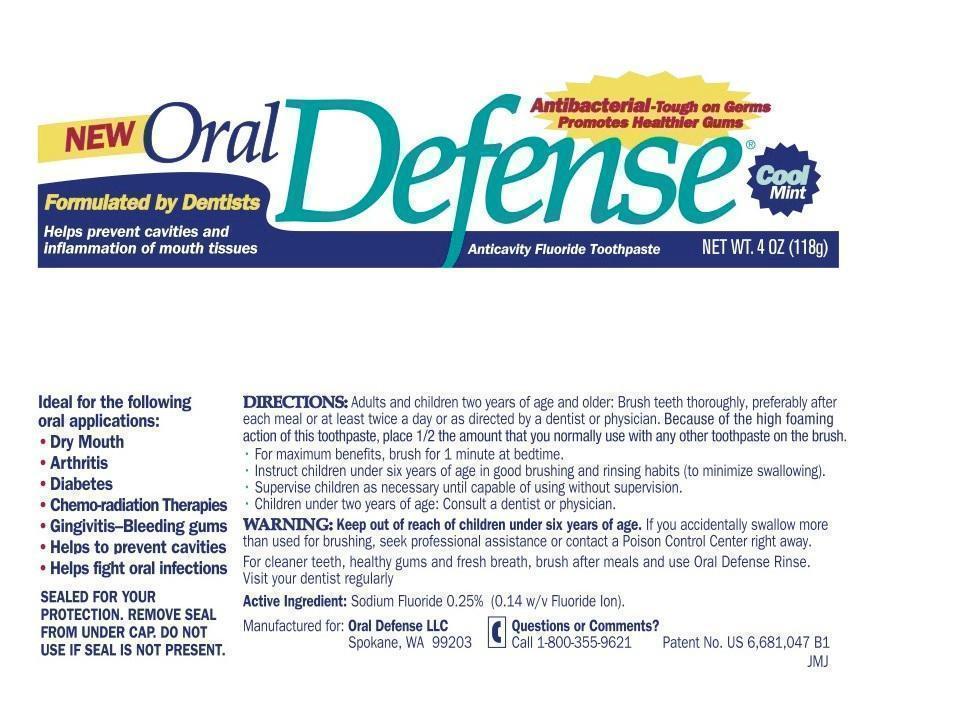 DRUG LABEL: Oral Defense
NDC: 52644-003 | Form: PASTE, DENTIFRICE
Manufacturer: Oral Defense
Category: otc | Type: HUMAN OTC DRUG LABEL
Date: 20130105

ACTIVE INGREDIENTS: SODIUM FLUORIDE .14 g/118 g
INACTIVE INGREDIENTS: GLYCERIN; CARBOXYMETHYLCELLULOSE SODIUM; SORBITOL; water; HYDRATED SILICA; CETYLPYRIDINIUM; ANHYDROUS CITRIC ACID; SACCHARIN SODIUM; SODIUM DEHYDROACETATE; TITANIUM DIOXIDE; SODIUM LAUROYL SARCOSINATE

Purpose

Anti-Cavity toothpaste

Active Ingredient

Sodium Fluoride 0.25% (0.14 w/v Fluoride Ion)

Use

Aids in prevention of dental cavities and gingivitis.

Warnings

Children under two years of age: Consult a dentist or physician. If more than used for brushing is accidentally swallowed, get medical help or contact a Poison Control Center right away.

Directions

Adults and children 2 years of age and older: Brush teeth thoroughly, preferably after each meal or at least twice a day, or as directed by a dentist or doctor. Instruct children under 6 years of age in good brushing and rinsing habits (to minimize swallowing). Supervise children as necessary until capable of using without supervision.

For maximum benefits, brush for 1 minute at bedtime and use with Oral Defense Fluoride Rinse.

Question and Comments?

1-800-355-9621 • 1-509-326-6693 Office

Manufactured for: Oral Defense LLC, P.O. Box 8267 Spokane, WA 99203

Patent No. US 6,861,047B

Inactive Ingredients

Sorbitol, Purified Water, Glycerin, Hydrated Silica, Sodium Lauroyl Sarconsinate, Cellulose Gum, Flavor, Titanium Dioxide, Cetylpyridinium Chloride, Citric Acid, Sodium Saccharin, FD&C Blue No. 1, Dehydroacetic Acid.